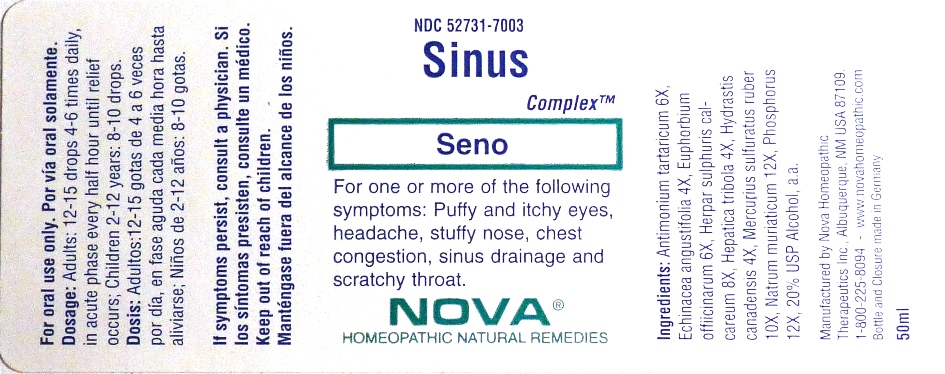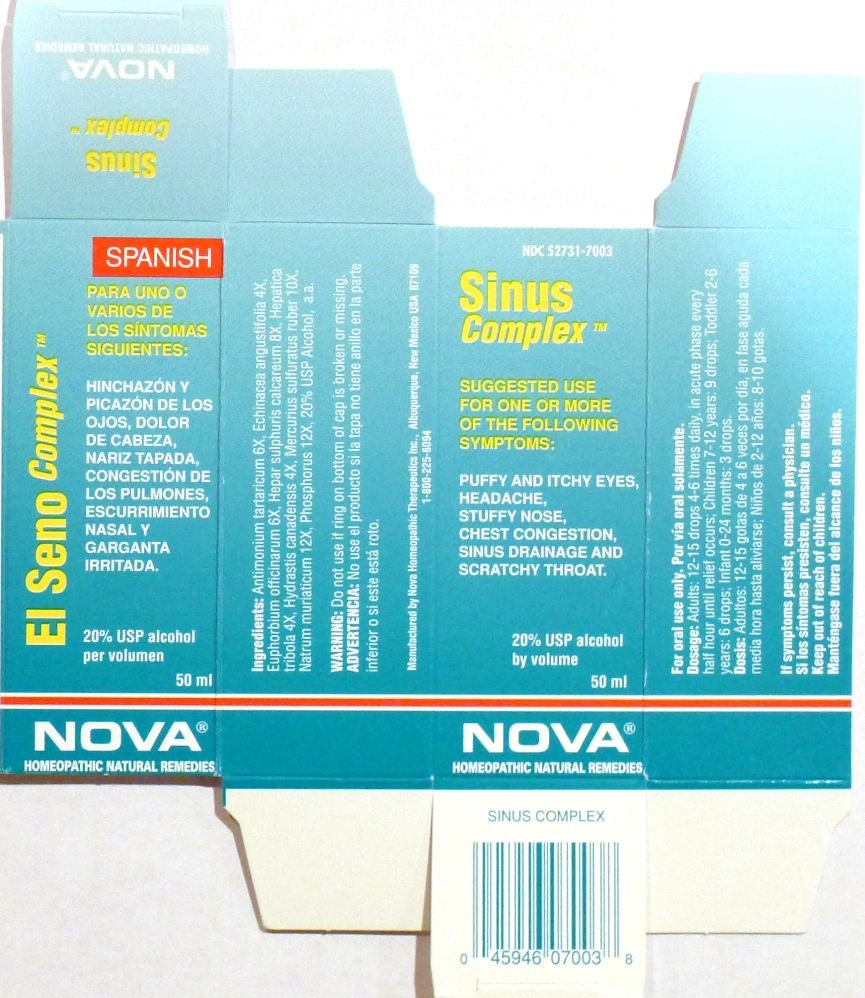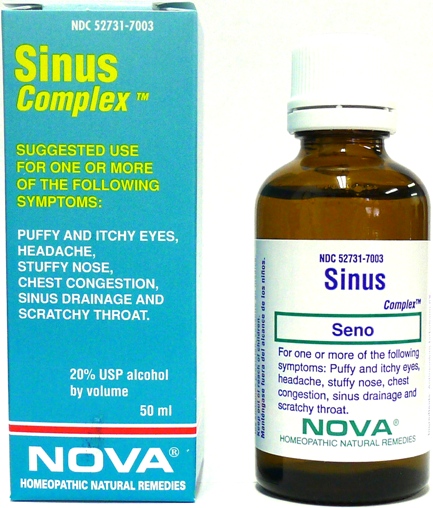 DRUG LABEL: Sinus Complex
NDC: 52731-7003 | Form: LIQUID
Manufacturer: Nova Homeopathic Therapeutics, Inc.
Category: homeopathic | Type: HUMAN OTC DRUG LABEL
Date: 20110601

ACTIVE INGREDIENTS: ANTIMONY POTASSIUM TARTRATE 6 [hp_C]/1 mL; ECHINACEA ANGUSTIFOLIA 4 [hp_X]/1 mL; EUPHORBIA RESINIFERA RESIN 6 [hp_X]/1 mL; CALCIUM SULFIDE 8 [hp_X]/1 mL; HEPATICA NOBILIS VAR. OBTUSA 4 [hp_X]/1 mL; GOLDENSEAL 4 [hp_X]/1 mL; MERCURIC SULFIDE 10 [hp_X]/1 mL; SODIUM CHLORIDE 12 [hp_X]/1 mL; PHOSPHORUS 12 [hp_X]/1 mL
INACTIVE INGREDIENTS: ALCOHOL

Sinus Complex

Purpose:

Suggested use for one or more of the following symptoms:
Puffy and itchy eyes, headache, stuffy nose, chest congestion, sinus drainage and scratchy throat.

Usage and Dosage:

For oral use only.

DOSAGE AND ADMINISTRATION

Adults:
In Acute Phase:
12-15 drops, every half hour until relief occurs
When Relief Occurs:
12-15 drops, 4-6 times per day
Children 2-12 years:
8-10 drops, 4-6 times per day

Warnings:

Keep out of reach of children.

WARNINGS

If symptoms persist, consult a physician.
Do not use if ring on bottom of cap is broken or missing.

Active Ingredients:

Antimonium tartaricum 6X, Echinacea angustifolia 4X, Euphorbium officinarum 6X, Hepar sulphuris calcareum 8X, Hepatica tribola 4X, Hydrastis canadensis 4X, Mercurius sulfuratus ruber 10X, Natrum muriaticum 12X, Phosphorus 12X

Inactive Ingredients:

Alcohol, 20% USP

QUESTIONS

Manufactured by Nova Homeopathic Therapeutics Inc., Albuquerque, New Mexico USA 87109
1-800-225-8094

PACKAGE LABEL

Sinus Complex Product

Sinus Complex Bottle Label

Sinus Complex Box